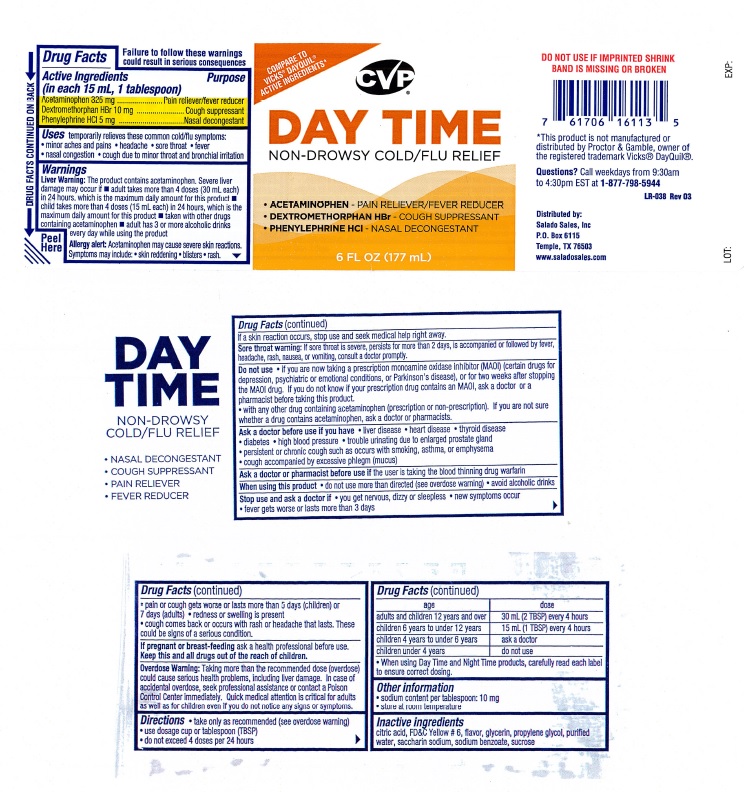 DRUG LABEL: Daytime
NDC: 57243-506 | Form: LIQUID
Manufacturer: Salado Sales, Inc.
Category: otc | Type: HUMAN OTC DRUG LABEL
Date: 20231229

ACTIVE INGREDIENTS: ACETAMINOPHEN 325 mg/15 mL; DEXTROMETHORPHAN HYDROBROMIDE 10 mg/15 mL; PHENYLEPHRINE HYDROCHLORIDE 5 mg/15 mL
INACTIVE INGREDIENTS: CITRIC ACID MONOHYDRATE; FD&C YELLOW NO. 6; GLYCERIN; PROPYLENE GLYCOL; WATER; SACCHARIN SODIUM; SODIUM BENZOATE; SUCROSE

Drug Facts Active Ingredients (in each 15 mL, 1 tablespoon)

Acetaminophen 325 mg
Dextromethorphan HBr 10 mg
Phenylephrine HCL 5 mg

Purpose
Pain reliever/fever reducer
Cough suppressant
Nasal decongestant

INDICATIONS AND USAGE

Uses temporarily relieves these common cold/flu symptoms:

- minor aches and pains ● headache ● sore throat ● fever
- nasal congestion ● cough due to minor throat and bronchial irritation

Warnings
Liver Warning: The product contains acetaminophen. Severe liver
damage may occur if ■ adult takes more than 4doses (30 mL each)
in 24 hours, which is the maximum daily amount for this product ■
child takes more than 4 doses (15 mL each) in 24 hours, which is the
maximum daily amount for this product ■ taken with other drugs
containing acetaminophen ■ adult has 3 or more alcoholic drinks
every day while using the product

Allergy alert: Acetaminophen may cause severe skin reactions.
Symptoms may include: • skin reddening • blisters • rash.

If a skin reaction occurs, stop use and seek medical help right away

Sore throat warning: If sore throat is severe, persists for more than 2 days, is accompanied or followed by fever,

headache, rash, nausea, or vomiting, consult a doctor promptly.

Do not use • If you are now taking a prescription monoamine oxidase inhibitor (MAOI) (certain drugs for

depression, psychiatric or emotional conditions, or Parkinson’s disease), or for two weeks after stopping

the MAOI drug. If you do not know if your prescription drug contains an MAOI, ask a doctor or a

pharmacist before taking this product.

• with any other drug containing acetaminophen (prescription or non-prescription). If you are not

sure whether a drug contains acetaminophen, ask a doctor or pharmacists.

Ask a doctor before use if you have • liver disease • heart disease •thyroid disease

- diabetes • high blood pressure • trouble urinating due to enlarged prostate gland
- persistent or chronic cough such as occurs with smoking, asthma, or emphysema
- cough accompanied by excessive phlegm (mucus)

Ask a doctor or pharmacist before use if the user is taking the blood thinning drug warfarin

When using this product •do not use more than directed (see overdose warning) • avoid alcoholic drinks

Stop use and ask a doctor if • you get nervous, dizzy, or sleepless • new symptoms occur
● fever gets worse or lasts more than 3 days
● pain or cough gets worse or lasts more than 5 days (children) or
7 days (adults) • redness or swelling is present
● cough comes back or occurs with rash or headache that lasts. These
could be signs of a serious condition.

PREGNANCY OR BREAST FEEDING

If pregnant of breast-feeding ask a health profesional before use.

KEEP OUT OF REACH OF CHILDREN

Keep this and all drugs out of the reach of children.

OVERDOSAGE

Overdose Warning: Taking more than the recommended dose (overdose)
could cause serious health problems, including liver damage. In case of
accidental overdose, seek professional assistance or contact a Poison
Control Center immediately. Quick medical attention is critical for adults
as well as for children even if you do not notice any signs or symptoms.

DOSAGE AND ADMINISTRATION

Directions ● take only as recommended (see overdose warning)

- use dosage cup or tablespoon (TBSP)
- do not exceed 4 doses per 24 hours

age dose

adults and children 12 years and over 30 mL (2 TBSP) every 4 hours

children 6 years to under 12 years 15 mL (1 TBSP) every 4 hours

children 4 years to under 6 years ask a doctor

children under 4 years do not use

- When using Day Time and Night Time products, carefully read each label to ensure correct dosing.

Other information

- sodium content per tablespoon: 10 mg
- store at room temperature

Inactive ingredients

citric acid, FD&C Yellow #6, flavor, glycerin, propylene glycol, purified

water, saccharin sodium, sodium benzoate, sucrose

Day Time product label

COMPARE TO

VICKS® DAYQUIL®

ACTIVE INGREDIENTS

CVP®

DAY TIME

NON-DROWSY COLD/FLU RELIEF

Acetaminophen……Pain Reliever/Fever Reducer
Dextromethorphan HBr……Cough Suppressant
Phenylephrine HCL ……. Nasal Decongestant

6 FL OZ (177 mL)

Failure to follow these warnings could result in serious consequences

DO NOT USE IF IMPRINTED SHRINK BAND IS MISSING OR BROKEN

*This product is not manufactured or
distributed by Proctor and Gamble, owner of
the registered trademark Vicks® Dayquil®.

Questions? Call weekdays from 9:30am
to 4:30pm EST at 1-877-798-5944

LR-038 Rev 03

Distributed by:
Salado Sales, Inc.
P.O. Box 6115
Temple, Tx 76503

www.saladosales.com

LOT: EXP:

RES